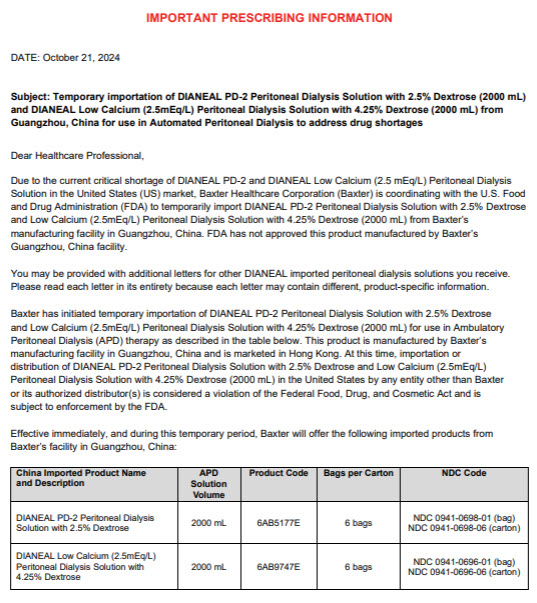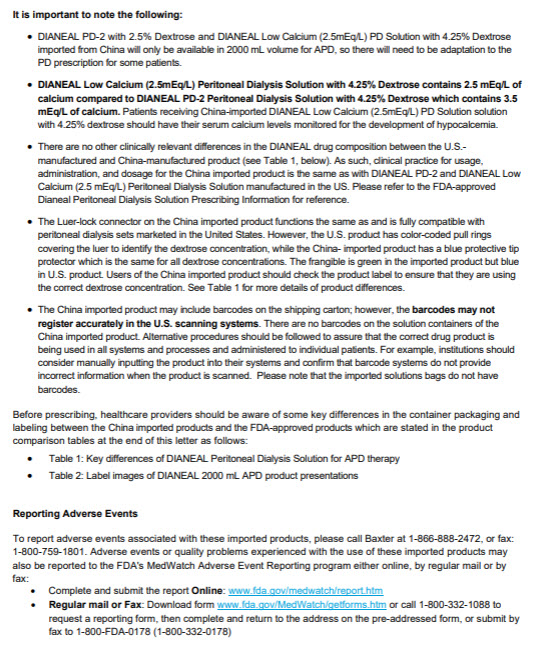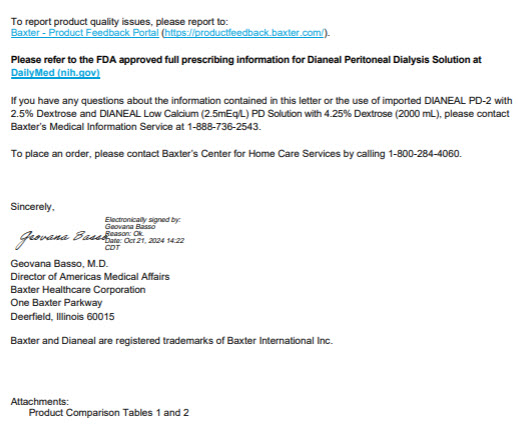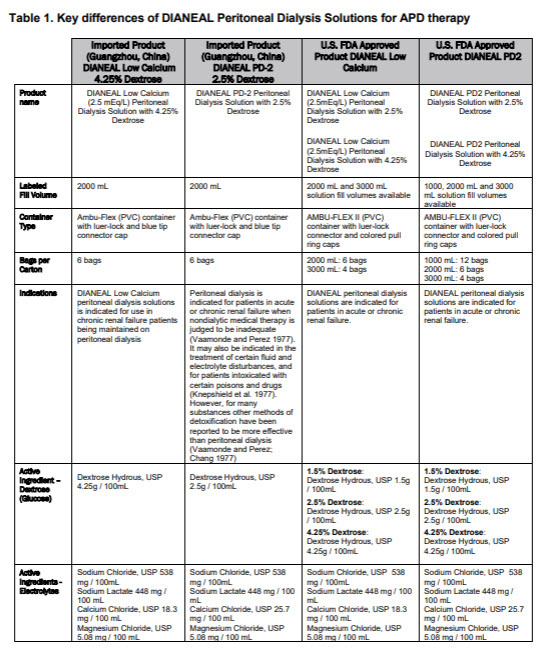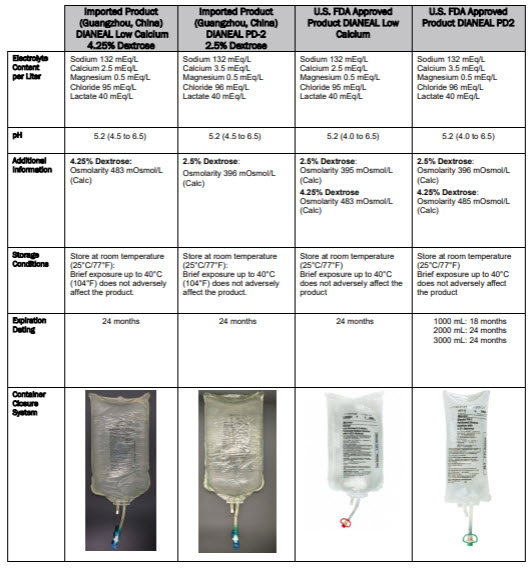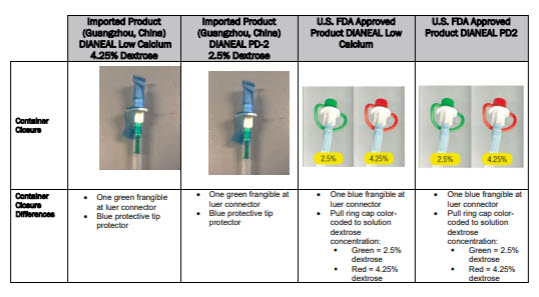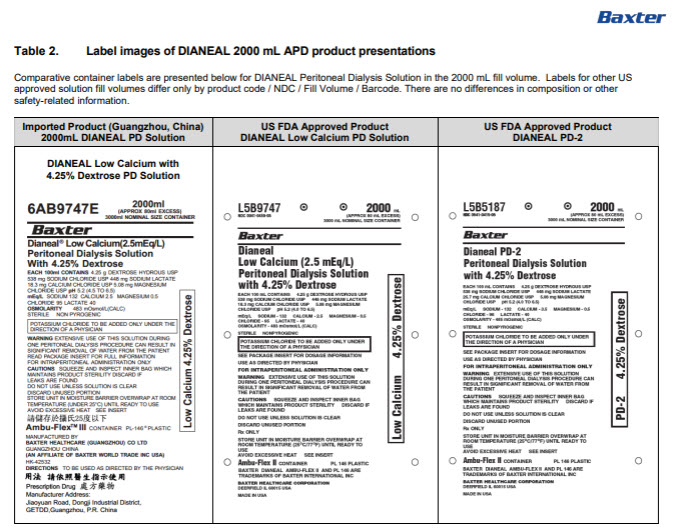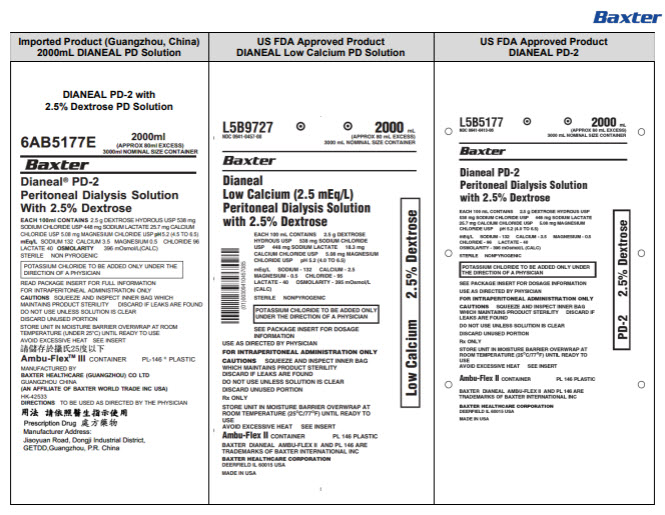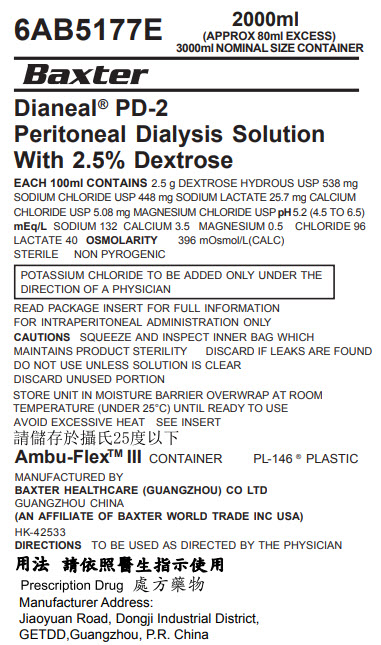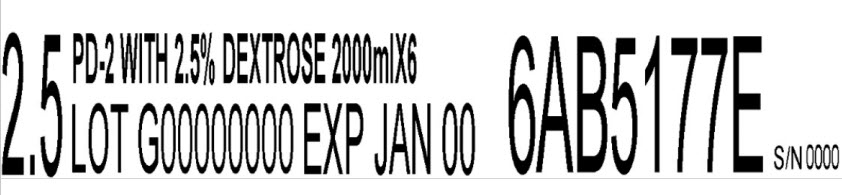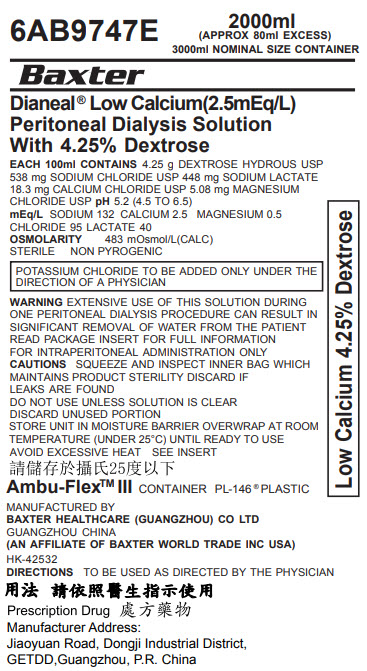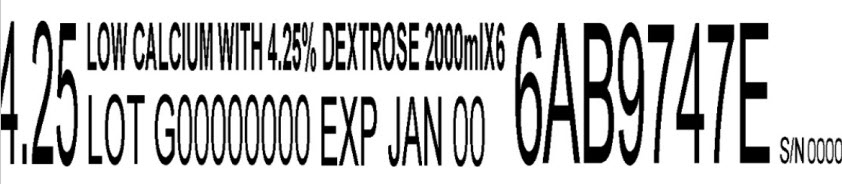 DRUG LABEL: DIANEAL LOW CALCIUM WITH DEXTROSE
NDC: 0941-0696 | Form: INJECTION, SOLUTION
Manufacturer: Vantive US Healthcare LLC
Category: prescription | Type: HUMAN PRESCRIPTION DRUG LABEL
Date: 20250508

ACTIVE INGREDIENTS: DEXTROSE MONOHYDRATE 4.25 g/100 mL; SODIUM CHLORIDE 538 mg/100 mL; SODIUM LACTATE 448 mg/100 mL; CALCIUM CHLORIDE 18.3 mg/100 mL; MAGNESIUM CHLORIDE 5.08 mg/100 mL
INACTIVE INGREDIENTS: WATER

DIANEAL with Dextrose

PACKAGE/LABEL PRINCIPAL DISPLAY PANEL

6AB5177E 2000ml
(APPROX 80ml EXCESS)
3000ml NOMINAL SIZE CONTAINER

BaxterLogo

Dianeal® PD-2
Peritoneal Dialysis Solution
With 2.5% Dextrose

EACH 100ml CONTAINS2.5 g DEXTROSE HYDROUS USP 538 mg
SODIUM CHLORIDE USP 448 mg SODIUM LACTATE 25.7 mg CALCIUM
CHLORIDE USP 5.08 mg MAGNESIUM CHLORIDE USP pH5.2 (4.5 to 6.5)
mEq/LSODIUM 132 CALCIUM 3.5 MAGNESIUM 0.5 CHLORIDE 96
LACTATE 40 OSMOLARITY396 mOsmol/L(CALC)
STERILE NON PYROGENIC

POTASSIUM CHLORIDE TO BE ADDED ONLY UNDER THE
DIRECTION OF A PHYSICIAN

READ PACKAGE INSERT FOR FULL INFORMATION
FOR INTRAPERITONEAL ADMINISTRATION ONLY
CAUTIONSSQUEEZE AND INSPECT INNER BAG WHICH
MAINTAINS PRODUCT STERILITY DISCARD IF LEAKS ARE FOUND
DO NOT USE UNLESS SOLUTION IS CLEAR
DISCARD UNUSED PORTION

STORE UNIT IN MOISTURE BARRIER OVERWRAP AT ROOM
TEMPERATURE (UNDER 25°C) UNTIL READY TO USE
AVOID EXCESSIVE HEAT SEE INSERT

Ambu-FlexTMIII CONTAINER PL-146 ® PLASTIC

MANUFACTURED BY
BAXTER HEALTHCARE (GUANGZHOU) CO LTD
GUANGZHOU CHINA
(AN AFFILIATE OF BAXTER WORLD TRADE INC USA)

HK-42533
DIRECTIONSTO BE USED AS DIRECTED BY THE PHYSICIAN

Prescription Drug
Manufacturer Address:
Jiaoyuan Road, Dongji Industrial District,
GETDD, Guangzhou, P.R. China

2.5 PD-2 WITH 2.5% DEXTROSE 2000mlX6
LOT G00000000 EXP JAN 00
6AB5177E
S/N 0000

6AB9747E 2000ml
(APPROX 80ml EXCESS)
3000ml NOMINAL SIZE CONTAINER

BaxterLogo

Dianeal® Low Calcium(2.5mEq/L)
Peritoneal Dialysis Solution
With 4.25% Dextrose

EACH 100ml CONTAINS4.25 g DEXTROSE HYDROUS USP
538 mg SODIUM CHLORIDE USP 448 mg SODIUM LACTATE
18.3 mg CALCIUM CHLORIDE USP 5.08 mg MAGNESIUM
CHLORIDE USP pH5.2 (4.5 to 6.5)
mEq/LSODIUM 132 CALCIUM 2.5 MAGNESIUM 0.5
CHLORIDE 95 LACTATE 40
OSMOLARITY483 mOsmol/L(CALC)
STERILE NON PYROGENIC

POTASSIUM CHLORIDE TO BE ADDED ONLY UNDER THE
DIRECTION OF A PHYSICIAN

WARNINGEXTENSIVE USE OF THIS SOLUTION DURING
ONE PERITONEAL DIALYSIS PROCEDURE CAN RESULT IN
SIGNIFICANT REMOVAL OF WATER FROM THE PATIENT
READ PACKAGE INSERT FOR FULL INFORMATION
FOR INTRAPERITONEAL ADMINISTRATION ONLY
CAUTIONSSQUEEZE AND INSPECT INNER BAG WHICH
MAINTAINS PRODUCT STERILITY DISCARD IF
LEAKS ARE FOUND
DO NOT USE UNLESS SOLUTION IS CLEAR
DISCARD UNUSED PORTION
STORE UNIT IN MOISTURE BARRIER OVERWRAP AT ROOM
TEMPERATURE (UNDER 25°C) UNTIL READY TO USE
AVOID EXCESSIVE HEAT SEE INSERT

Ambu-FlexTMIII CONTAINER PL-146®PLASTIC

MANUFACTURED BY
BAXTER HEALTHCARE (GUANGZHOU) CO LTD
GUANGZHOU CHINA
(AN AFFILIATE OF BAXTER WORLD TRADE INC USA)

HK-42532
DIRECTIONSTO BE USED AS DIRECTED BY THE PHYSICIAN

Prescription Drug
Manufacturer Address:
Jiaoyuan Road, Dongji Industrial District,
GETDD, Guangzhou, P.R. China

4.25 LOW CALCIUM WITH 4.25% DEXTROSE 2000mlX6
LOT G00000000 EXP JAN 00
6AB9747E
S/N 0000